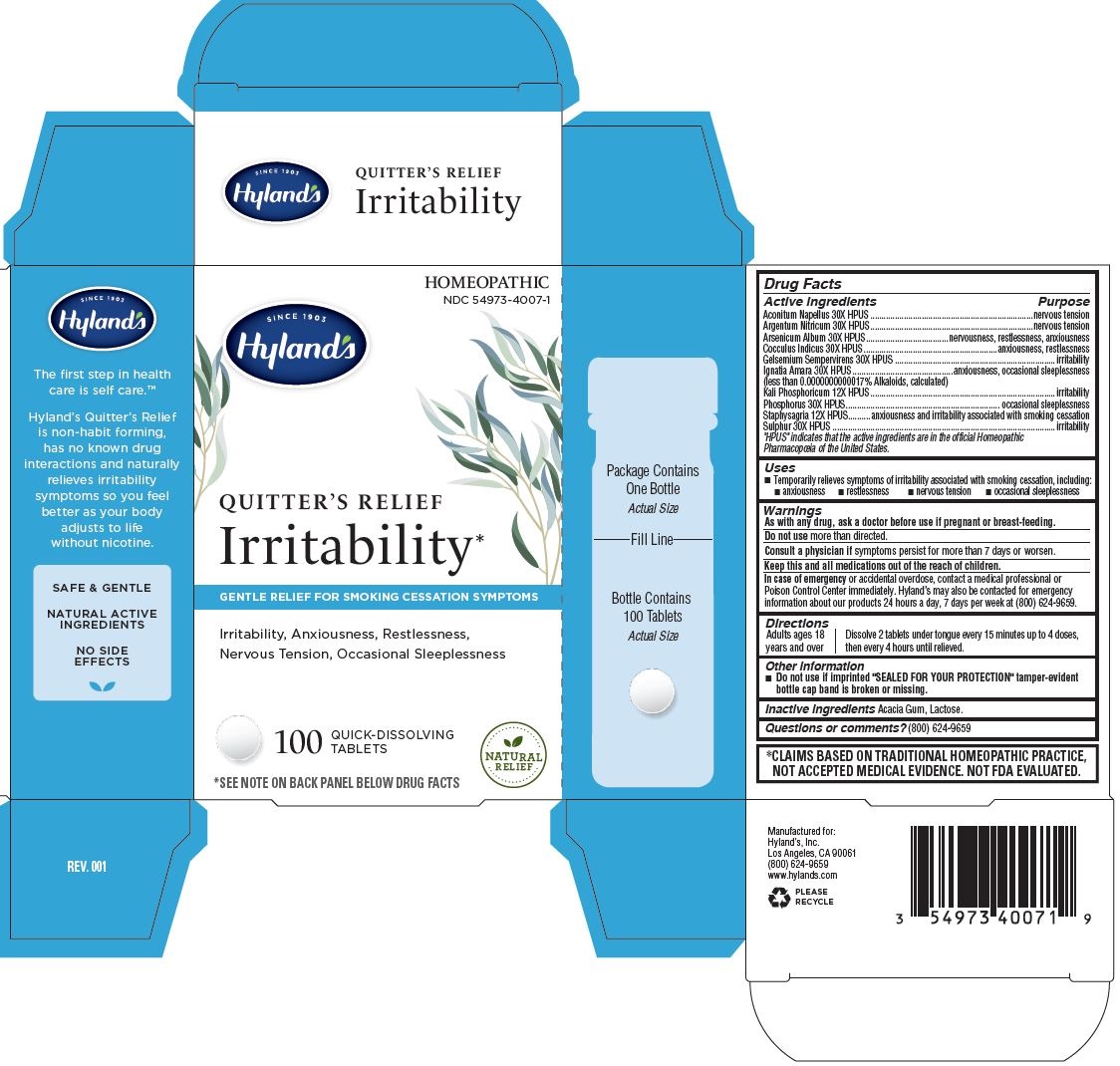 DRUG LABEL: Quitters Relief Irritability
NDC: 54973-4007 | Form: TABLET
Manufacturer: Hyland's Inc.
Category: homeopathic | Type: HUMAN OTC DRUG LABEL
Date: 20221213

ACTIVE INGREDIENTS: SILVER NITRATE 30 [hp_X]/1 1; SULFUR 30 [hp_X]/1 1; ACONITUM NAPELLUS WHOLE 30 [hp_X]/1 1; ARSENIC TRIOXIDE 30 [hp_X]/1 1; ANAMIRTA COCCULUS SEED 30 [hp_X]/1 1; DIBASIC POTASSIUM PHOSPHATE 12 [hp_X]/1 1; GELSEMIUM SEMPERVIRENS ROOT 30 [hp_X]/1 1; STRYCHNOS IGNATII SEED 30 [hp_X]/1 1; DELPHINIUM STAPHISAGRIA SEED 12 [hp_X]/1 1; PHOSPHORUS 30 [hp_X]/1 1
INACTIVE INGREDIENTS: LACTOSE MONOHYDRATE; ACACIA

Hyland’s Quitter’s Relief Irritability

PURPOSE

Temporarily relieves symptoms of irritability associated with smoking cessation, including: anxiousness, restlessness, nervous, tension, occasional sleeplessness

Drug Facts

Active ingredients

Active ingredients | Purpose
Aconitum Napellus 30X HPUS | nervous tension
Argentum Nitricum 30X HPUS | nervous tension
Arsenicum Album 30X HPUS | nervousness, restlessness, anxiousness
Cocculus Indicus 30X HPUS | anxiousness, restlessness
Gelsemium Sempervirens 30X HPUS | irritability
Ignatia Amara 30X HPUS; (less than 0.0000000000017% Alkaloids, calculated) | anxiousness, occasional sleeplessness
Kali Phosphoricum 12X HPUS | irritability
Phosphorus 30X HPUS | occasional sleeplessness
Staphysagria 12X HPUS | anxiousness and irritability associated with smoking cessation
Sulphur 30X HPUS | irritability

"HPUS" indicates that the active ingredients are in the official Homeopathic Pharmacopoeia of the United States.

Uses

■ Temporarily relieves symptoms of irritability associated with smoking cessation, including:

■ anxiousness ■ restlessness ■ nervous tension ■ occasional sleeplessness

Warnings

PREGNANCY OR BREAST FEEDING

As with any drug, ask a doctor before use if pregnant or breast-feeding.

Do not use more than directed.

ASK DOCTOR

Consult a physician if symptoms persist for more than 7 days or worsen.

KEEP OUT OF REACH OF CHILDREN

Keep this and all medications out of the reach of children.

OVERDOSAGE

In case of emergency or accidental overdose, contact a medical professional or Poison Control Center immediately. Hyland’s may also be contacted for emergency information about our products 24 hours a day, 7 days per week at (800) 624-9659.

Directions

Adults ages 18

years and over

Dissolve 2 tablets under tongue every 15 minutes up to 4 doses,

then every 4 hours until relieved.

Other information

■ Do not use if imprinted "SEALED FOR YOUR PROTECTION" tamper-evident bottle cap band is broken or missing.

Inactive ingredients

Acacia Gum, Lactose.

Questions or comments?

(800) 624-9659

*CLAIMS BASED ON TRADITIONAL HOMEOPATHIC PRACTICE, NOT ACCEPTED MEDICAL EVIDENCE. NOT FDA EVALUATED.

PACKAGE LABEL - PRINCIPAL DISPLAY PANEL

HOMEOPATHIC

NDC 54973-4007-1

SINCE 1903

Hyland's

QUITTER’S RELIEF

Irritability*

GENTLE RELIEF FOR SMOKING CESSATION SYMPTOMS

Irritability, Anxiousness, Restlessness,

Nervous Tension, Occasional Sleeplessness

100 QUICK-DISSOLVING

TABLETS

NATURAL

RELIEF

*SEE NOTE ON BACK PANEL BELOW DRUG FACTS